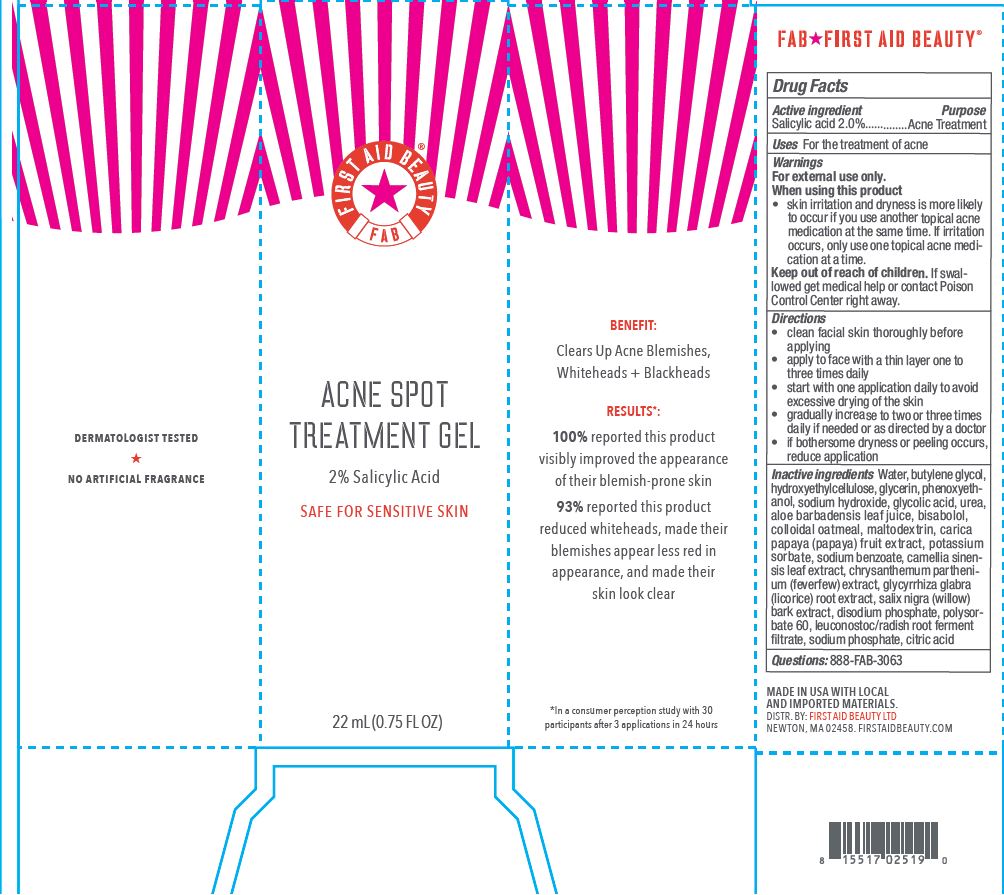 DRUG LABEL: First Aid Beauty FAB Acne Spot Treatment
NDC: 69423-724 | Form: GEL
Manufacturer: The Procter & Gamble Manufacturing Company
Category: otc | Type: HUMAN OTC DRUG LABEL
Date: 20251218

ACTIVE INGREDIENTS: SALICYLIC ACID 2 g/100 mL
INACTIVE INGREDIENTS: HYDROXYETHYL CELLULOSE, UNSPECIFIED; SODIUM HYDROXIDE; GLYCOLIC ACID; ALOE VERA LEAF; OATMEAL; BUTYLENE GLYCOL; PHENOXYETHANOL; UREA; LEVOMENOL; TANACETUM PARTHENIUM FLOWER; GLYCYRRHIZA GLABRA; LEUCONOSTOC/RADISH ROOT FERMENT FILTRATE; SODIUM PHOSPHATE; GREEN TEA LEAF; POLYSORBATE 60; WATER; GLYCERIN; CITRIC ACID MONOHYDRATE; POTASSIUM SORBATE; SODIUM BENZOATE; MALTODEXTRIN; PAPAYA; SALIX NIGRA BARK; SODIUM PHOSPHATE, DIBASIC, ANHYDROUS

First Aid Beauty FAB Acne Spot Treatment Gel

Drug Facts

Active ingredients

Salicylic Acid 2%

Purpose

Acne Treatment

Uses

- for the treatment of acne

Warnings

For external use only.

When using this product

- Skin irritation and dryness is more likely to occur if you use another topical acne medication at the same time. If irritation occurs, only use one topical acne medication at a time.
- avoid contact with eyes. If contact occurs, rinse eyes thoroughly with water.

Stop use and ask a doctor if skin irritation occurs/gets worse.

Keep out of reach of children. If swallowed, get medical help or contact a Poison Control Center right away.

Directions

- clean facial skin thoroughly before applying
- apply to face with a thin layer one to three tim es daily
- start with one application daily to avoid excessive drying of the skin
- gradually increase to two or three times daily if needed or as directed by a doctor
- if bothersome dryness or peeling occurs, reduce application

INACTIVE INGREDIENT

Water, butylene glycol, hydroxyethylcellulose,glycerin, phenoxyethanol, sodium hydroxide, glycolic acid, urea, aloe barbadensis leaf juice, bisabolol, colloidal oatmeal, maltodextrin, carica papaya (papaya) fruit extract, potassium sorbate, sodium benzoate, camellia sinensis leaf extract, chrysanthemum parthenium (feverfew) extract, glycyrrhiza glabra (licorice) root extract, salix nigra (willow) bark extract, disodium phosphate, polysorbate 60, leuconostoc/radish root ferment filtrate, sodium phosphate, citric acid

Questions:

888-FAB-3063

MADE IN USA

FIRST AID BEAUTY LTD

NEWTON, MA 02458

WWW.FIRSTAIDBEAUTY.COM

PRINCIPAL DISPLAY PANEL - 22 mL carton

FIrst Aid Beauty ®

FAB

ACNE SPOT

TREATMENT GEL

2% Salicylic Acid

Safe for sensitive skin

22 mL (0.75 FL OZ)